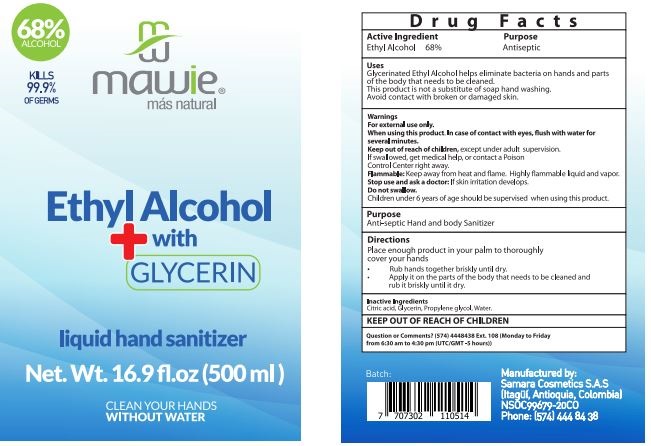 DRUG LABEL: Hand Sanitizer
NDC: 79894-002 | Form: LIQUID
Manufacturer: SAMARA COSMETICS S.A.S.
Category: otc | Type: HUMAN OTC DRUG LABEL
Date: 20200729

ACTIVE INGREDIENTS: ALCOHOL 68 mg/1 mL
INACTIVE INGREDIENTS: CITRIC ACID MONOHYDRATE; WATER; PROPANEDIOL; GLYCERIN

Hand Sanitizer

Uses

* Helps eliminate bacterias on the hand and parts of the body that needs to be cleaned. This product is not a substitute of soap hand washing. Avoid contact with broken or damaged skin

Active Ingredient

Active Ingredient Purpose

- Ethyl Alcohol 68%...................................Antiseptic

Warnings

- For external use only-
- When using this product keep out o f eyes. In case of contact, flush with water several minutes.
- Keep out of reach of children except under adult supervision
- If swalow get medical help or contact a Poison Control Center right away.
- Flammable: Keep away from heat and flame.
- Stop use and ask Doctor: if skin irritation develops.
- Do not swalow
- Children under 6 years old should be supervised when using this product

Stop use and ask a doctor if

* Irritation develops

Keep out of reach of children. In case of incidental ingestion, see professional advice or contact a Poison Control Center inmediately.

Directions

- Place enough product in your palm to throughly cover your hands.
- Rub hands together briskly until dry
- Apply it on the parts of the body that needs to be cleaned and rub it briskly until dry

Inactive Ingredients

Water, citric acid, glycerine, propylene glycol

Questions?

QUESTIONS OR COMMENTS: (574) 4448438 Ext 108 (Monday to Friday) 6:30 am to 4:30 pm (UTC/GMT 5 hours)

Uses

* Helps eliminate bacteria on the hand and parts of the body that needs to be cleaned. This product is not a substitute of soap hand washing. Avoid contact with broken or damaged skin